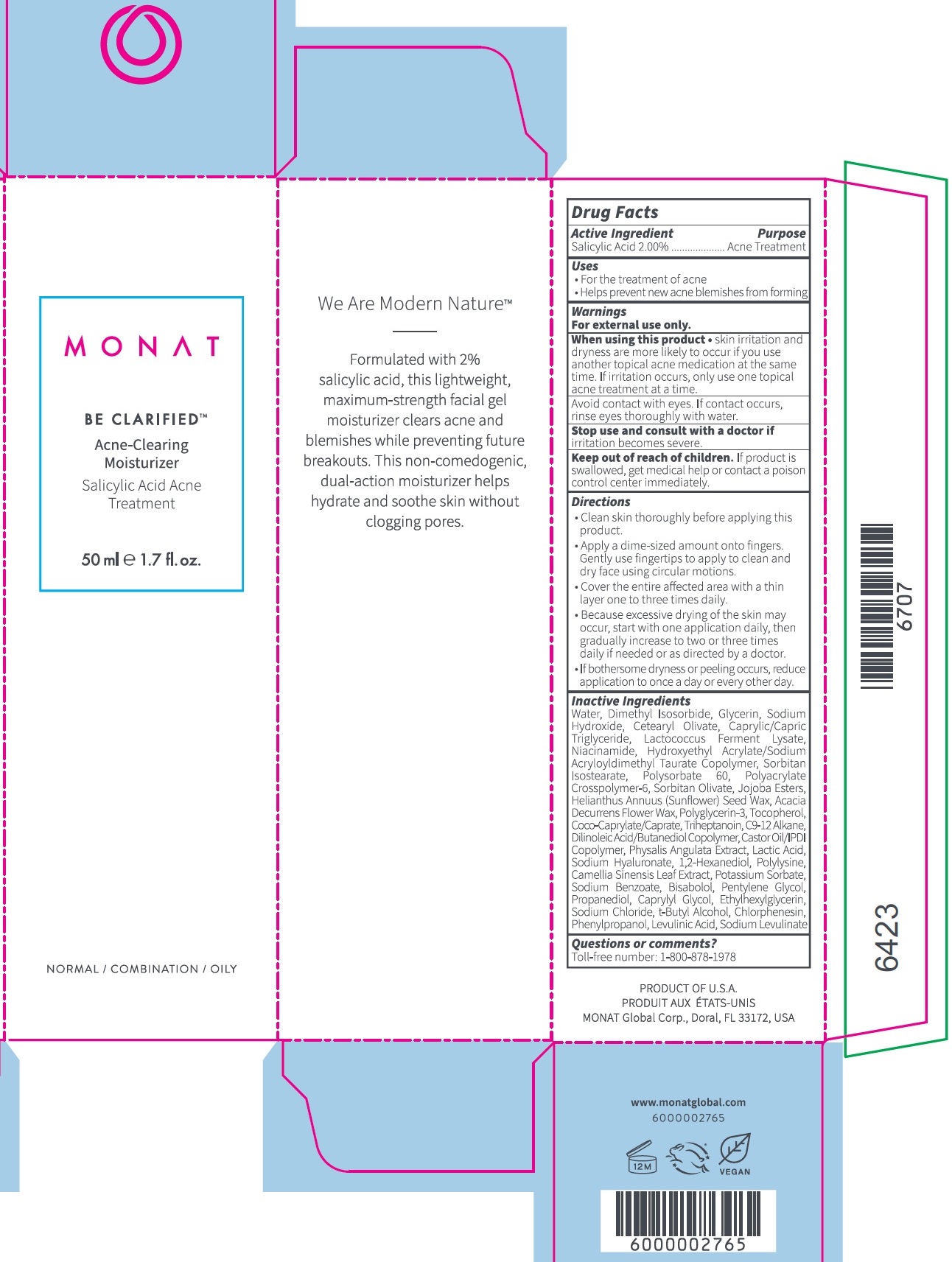 DRUG LABEL: Monat Be Clarified Acne-Clearing Moisturizer
NDC: 68577-107 | Form: LOTION
Manufacturer: Cosmax Usa, Corporation
Category: otc | Type: HUMAN OTC DRUG LABEL
Date: 20241226

ACTIVE INGREDIENTS: SALICYLIC ACID 20 mg/1 mL
INACTIVE INGREDIENTS: WATER; DIMETHYL ISOSORBIDE; GLYCERIN; SODIUM HYDROXIDE; CETEARYL OLIVATE; MEDIUM-CHAIN TRIGLYCERIDES; NIACINAMIDE; SORBITAN ISOSTEARATE; POLYSORBATE 60; AMMONIUM ACRYLOYLDIMETHYLTAURATE, DIMETHYLACRYLAMIDE, LAURYL METHACRYLATE AND LAURETH-4 METHACRYLATE COPOLYMER, TRIMETHYLOLPROPANE TRIACRYLATE CROSSLINKED (45000 MPA.S); SORBITAN OLIVATE; HELIANTHUS ANNUUS SEED WAX; ACACIA DECURRENS FLOWER WAX; POLYGLYCERIN-3; TOCOPHEROL; COCOYL CAPRYLOCAPRATE; TRIHEPTANOIN; DILINOLEIC ACID/BUTANEDIOL COPOLYMER; PHYSALIS ANGULATA WHOLE; LACTIC ACID, UNSPECIFIED FORM; HYALURONATE SODIUM; 1,2-HEXANEDIOL; GREEN TEA LEAF; POTASSIUM SORBATE; SODIUM BENZOATE; LEVOMENOL; PENTYLENE GLYCOL; PROPANEDIOL; CAPRYLYL GLYCOL; ETHYLHEXYLGLYCERIN; SODIUM CHLORIDE; TERT-BUTYL ALCOHOL; CHLORPHENESIN; PHENYLPROPANOL; LEVULINIC ACID; SODIUM LEVULINATE

Monat Be Clarified Acne-Clearing Moisturizer

Active Ingredient

Salicylic Acid 2.00%

Purpose

Acne Treatment

Uses

- For the treatment of acne
- Helps prevent new acne blemishes from forming

Warnings

For external use only.

When using this product

- skin irritation and dryness are more likely to occur if you use another topical acne medication at the same time. If irritation occurs, only use one topical acne treatment at a time.
  Avoid contact with eyes. If contact occurs, rinse eyes thoroughly with water.

Stop use and consult with a doctor if

irritation becomes severe.

Keep out of reach of children.

If product is swallowed, get medical help or contact a poison control center immediately.

Directions

- Clean skin thoroughly before applying this product.
- Apply a dime-sized amounth onto fingers. Gently use fingertips to apply to clean and dry face using circular motions.
- Cover the entire affected area with a thin layer one to three times daily.
- Because excessive drying of the skin may occur, start with one application daily, then gradually increase to two or three times daily if needed or as directed by a doctor.
- If bothersome dryness or peeling occurs, reduce application to once a day or every other day.

Inactive Ingredients

Water, Dimethyl Isosorbide, Glycerin, Sodium Hydroxide, Cetearyl Olivate, Caprylic/Capric Triglyceride, Lactococcus Ferment Lysate, Niacinamide, Hydroxyethyl Acrylate/Sodium Acryloydimethyl Taurate Copolymer, Sorbitan Isostearate, Polysorbate 60, Polyacrylate Crosspolymer-6, Sorbitan Olivate, Jojoba Esters, Helianthus Annuus (Sunflower) Seed Wax, Acacia Decurrens Flower Wax, Polyglycerin-3, Tocopherol, Coco-Caprylate/Caprate, Triheptanoin, C9-12 Alkane, Dilinoleic Acid/Butanediol Copolymer, Castor Oil/IPDI Copolymer, Physalis Angulata Extract, Lactic Acid, Sodium Hyaluronate, 1,2-Hexanediol, Polylysine, Camellia Sinensis Leaf Extract, Potassium Sorbate, Sodium Benzoate, Bisabolol, Pentylene Glycol, Propanediol, Caprylyl Glycol, Ethylhexylglycerin, Sodium Chloride, t-Butyl Alcohol, Chlorphenesin, Phenylpropanol, Levulinic Acid, Sodium Levulinate

Questions or comments?

Toll-free number: 1-800-878-1978